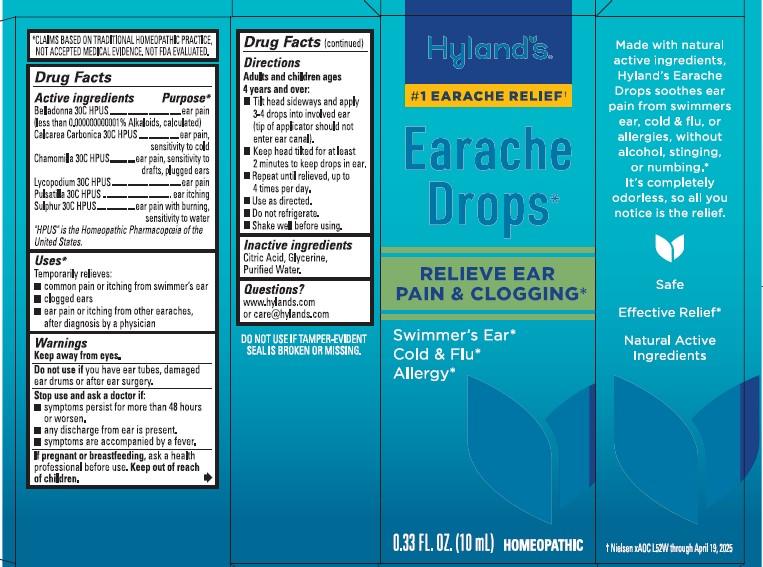 DRUG LABEL: Hylands Naturals Earache Drops
NDC: 54973-4124 | Form: LIQUID
Manufacturer: Hyland's Inc.
Category: homeopathic | Type: HUMAN OTC DRUG LABEL
Date: 20250827

ACTIVE INGREDIENTS: CHAMOMILE 30 [hp_C]/1 mL; LYCOPODIUM CLAVATUM SPORE 30 [hp_C]/1 mL; PULSATILLA PATENS WHOLE 30 [hp_C]/1 mL; SULFUR 30 [hp_C]/1 mL; CALCIUM CARBONATE 30 [hp_C]/1 mL; BELLADONNA LEAF 30 [hp_C]/1 mL
INACTIVE INGREDIENTS: GLYCERIN; WATER; CITRIC ACID MONOHYDRATE

Hyland's Earache Drops

Drug Facts

Active ingredients | Purpose*
Belladonna 30C HPUS (less than 0.000000000001% Alkaloids, calculated) | ear pain
Calcarea Carbonica 30C HPUS | ear pain, sensitivity to cold
Chamomilla 30C HPUS | ear pain, sensitivity to drafts, plugged ears
Lycopodium 30C HPUS | ear pain
Pulsatilla 30C HPUS | ear itching
Sulphur 30C HPUS | ear pain with burning, sensitivity to water

HPUS" is the Homeopathic Pharmacopoeia of the
United States.

Uses*

Temporarily relieves:
■ common pain or itching from swimmer’s ear
■ clogged ears
■ ear pain or itching from other earaches,
after diagnosis by a physician

Warnings

Keep away from eyes.

Do not use if you have ear tubes, damaged ear drums or after ear surgery.

Stop use and ask a doctor if:
■ symptoms persist for more than 48 hours or worsen.
■ any discharge from ear is present.
■ symptoms are accompanied by a fever.

PREGNANCY OR BREAST FEEDING

If pregnant or breastfeeding, ask a health professional before use.

Keep out of reach of children.

Drug Facts (continued)

Directions

Adults and children ages
4 years and over:
■ Tilt head sideways and apply
3-4 drops into involved ear
(tip of applicator should not
enter ear canal).
■ Keep head tilted for at least
2 minutes to keep drops in ear.
■ Repeat until relieved, up to
4 times per day.
■ Use as directed.
■ Do not refrigerate.
■ Shake well before using.

Inactive ingredients

Citric Acid, Glycerine, Purified Water.

Questions?

www.hylands.com
or care@hylands.com

DO NOT USE IF TAMPER-EVIDENT SEAL IS BROKEN OR MISSING.

PURPOSE

Temporarily relieves: common pain or itching from swimmer’s ear, clogged ears, ear pain or itching from other earaches, after diagnosis by a physician

Principal Display Panel

Hyland's

Earache Drops 0.33 FL. OZ. (10 mL)